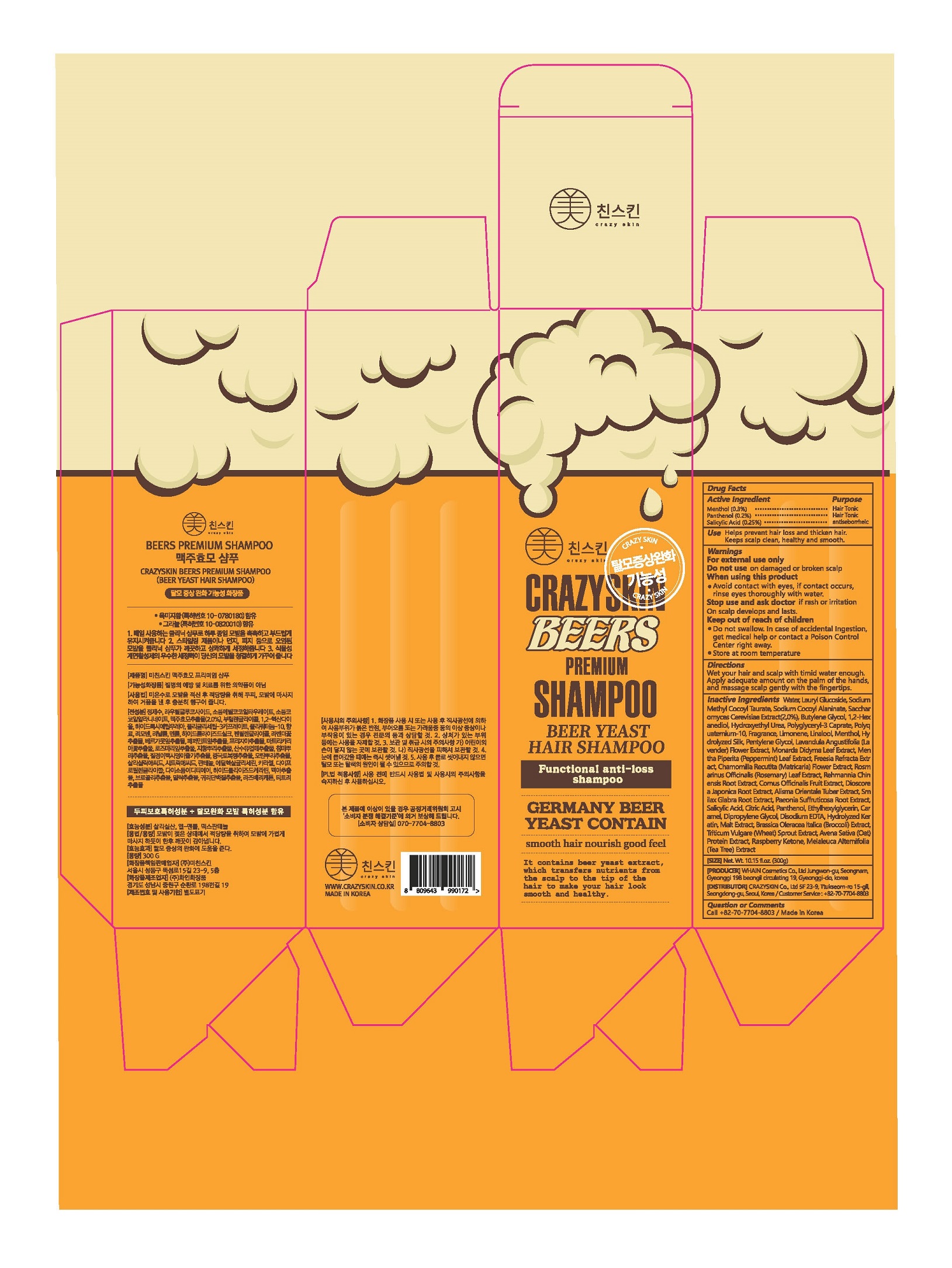 DRUG LABEL: CRAZYSKIN BEERS PREMIUM
NDC: 73643-0002 | Form: SHAMPOO
Manufacturer: Crazy Skin Co., Ltd.
Category: otc | Type: HUMAN OTC DRUG LABEL
Date: 20201205

ACTIVE INGREDIENTS: LEVOMENTHOL 0.3 g/100 g; SALICYLIC ACID 0.25 g/100 g; DEXPANTHENOL 0.2 g/100 g
INACTIVE INGREDIENTS: WATER

ACTIVE INGREDIENT

L-menthol, dexpanthenol, salicylic acid

INACTIVE INGREDIENT

Water
Lauryl Glucoside
Sodium Methyl Cocoyl Taurate
Sodium Cocoyl Alaninate
Saccharomyces Cerevisiae Extract
Butylene Glycol
1,2-Hexanediol
Hydroxyethyl Urea
Polyglyceryl-3 Caprate
Polyquaternium-10
Fragrance
Limonene
Linalool
Hydrolyzed Silk
Pentylene Glycol
Lavandula Angustifolia (Lavender) Flower Extract
Monarda Didyma Leaf Extract
Mentha Piperita (Peppermint) Leaf Extract
Freesia Refracta Extract
Chamomilla Recutita (Matricaria) Flower Extract
Rosmarinus Officinalis (Rosemary) Leaf Extract
Rehmannia Chinensis Root Extract
Cornus Officinalis Fruit Extract
Dioscorea Japonica Root Extract
Alisma Orientale Tuber Extract
Smilax Glabra Root Extract
Paeonia Suffruticosa Root Extract
Citric Acid
Ethylhexylglycerin
Caramel
Dipropylene Glycol
Disodium EDTA
Hydrolyzed Keratin
Malt Extract
Brassica Oleracea Italica (Broccoli) Extract
Triticum Vulgare (Wheat) Sprout Extract
Avena Sativa (Oat) Protein Extract
Raspberry Ketone
Melaleuca Alternifolia (Tea Tree) Extract

PURPOSE

Helps prevent hair loss and thicken hair, keeps scalp clean, healthy and smooth

do not use on damaged or broken scalp

when using this product

avoid contact with eyes, if contact occurs, rinse eyes thoroughly with water

stop use and ask doctor if rash or irritation on scalp develops and lasts

Keep Out of Reach of Children

DOSAGE AND ADMINISTRATION

wet your hair and scalp with timid water enough

apply adequate amount on the palm of the hands, and massage scalp gently with the fingertips

INDICATIONS AND USAGE

Helps prevent hair loss and thicken hair,

Keep scalp clean, healthy and smooth